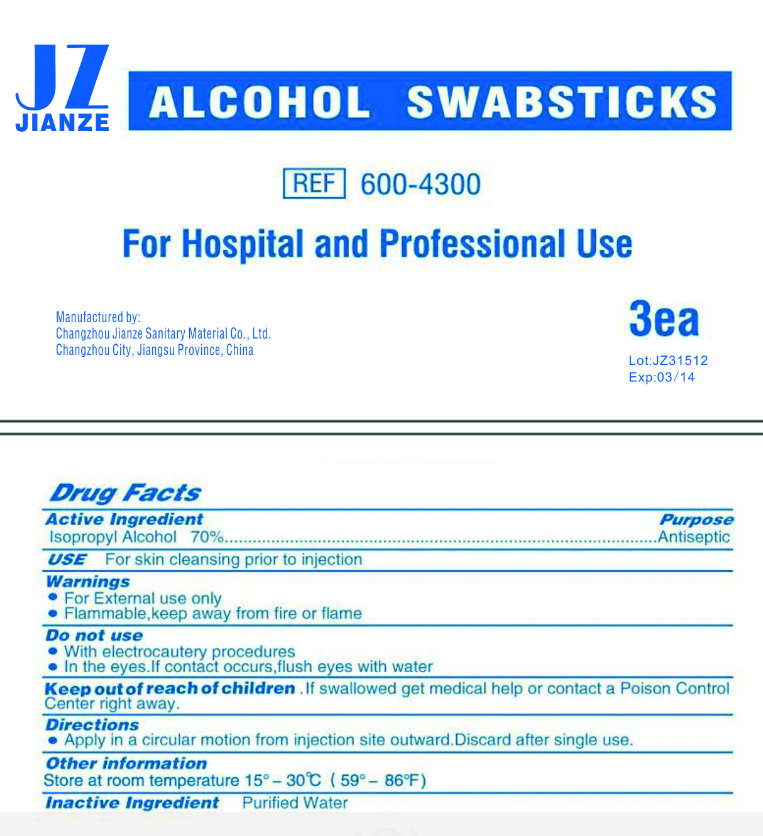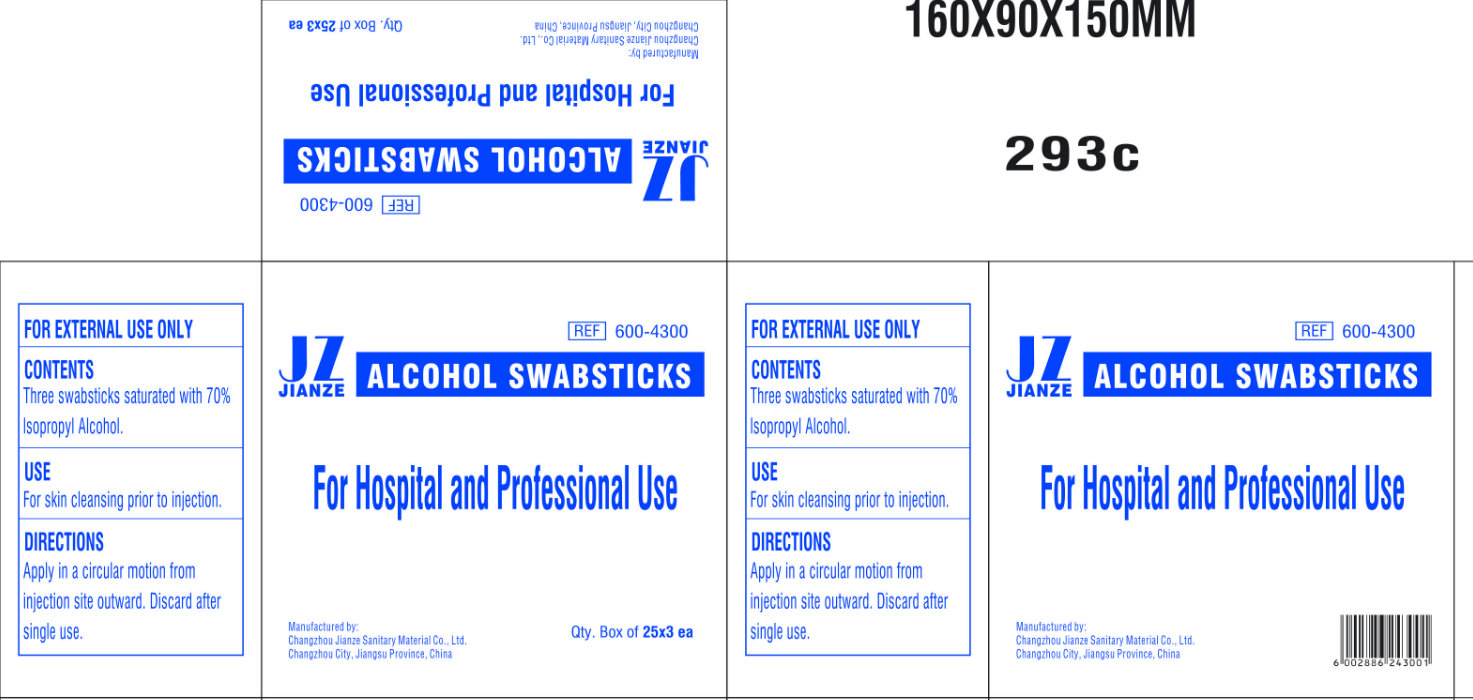 DRUG LABEL: JIANZE ALCOHOL
NDC: 50666-004 | Form: SWAB
Manufacturer: Changzhou Jianze Sanitary Material Co., Ltd.
Category: otc | Type: HUMAN OTC DRUG LABEL
Date: 20120606

ACTIVE INGREDIENTS: ISOPROPYL ALCOHOL 70 mL/100 mL
INACTIVE INGREDIENTS: WATER

JIANZE ALCOHOL SWABSTICKS

Active Ingredient

Isopropyl Alcohol 70%

Purpose

Antiseptic

Use

For skin cleansing prior to injection

Warnings

- For external use only
- Flammable, keep away from fire or flame

Do Not Use

- with electrocautery procedures
- In the eyes. If contact occurs, flush with water

Keep out of reach of children

If swallowed get medical help or contact a Poison Control Center right away.

Directions

- Apply in a circular motion from injection site outward. Discard after single use.

Other Information

Store at room temperature 15 degrees - 30 degrees C (59 degrees - 86 degrees F)

Inactive Ingredient

Purified water